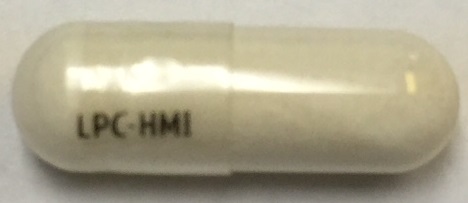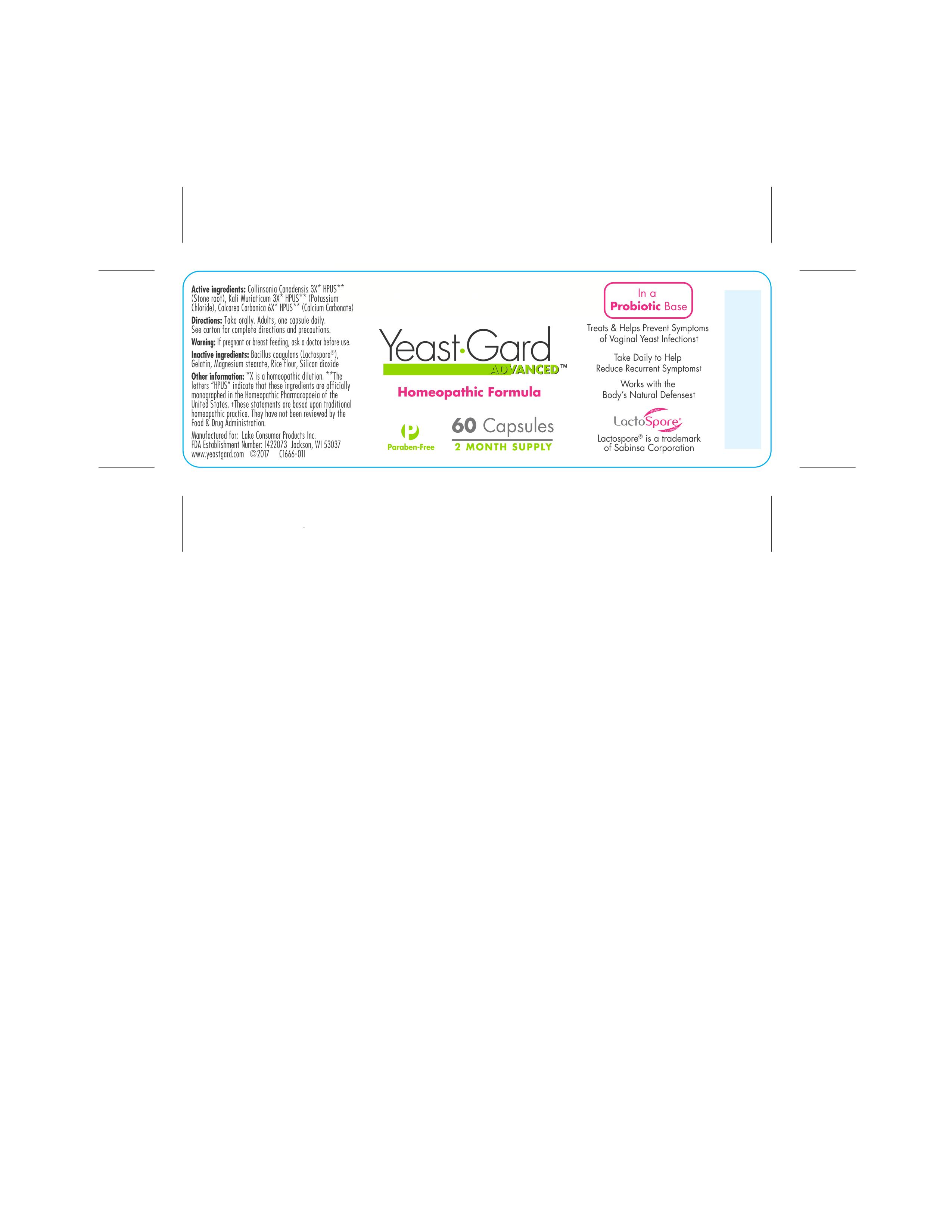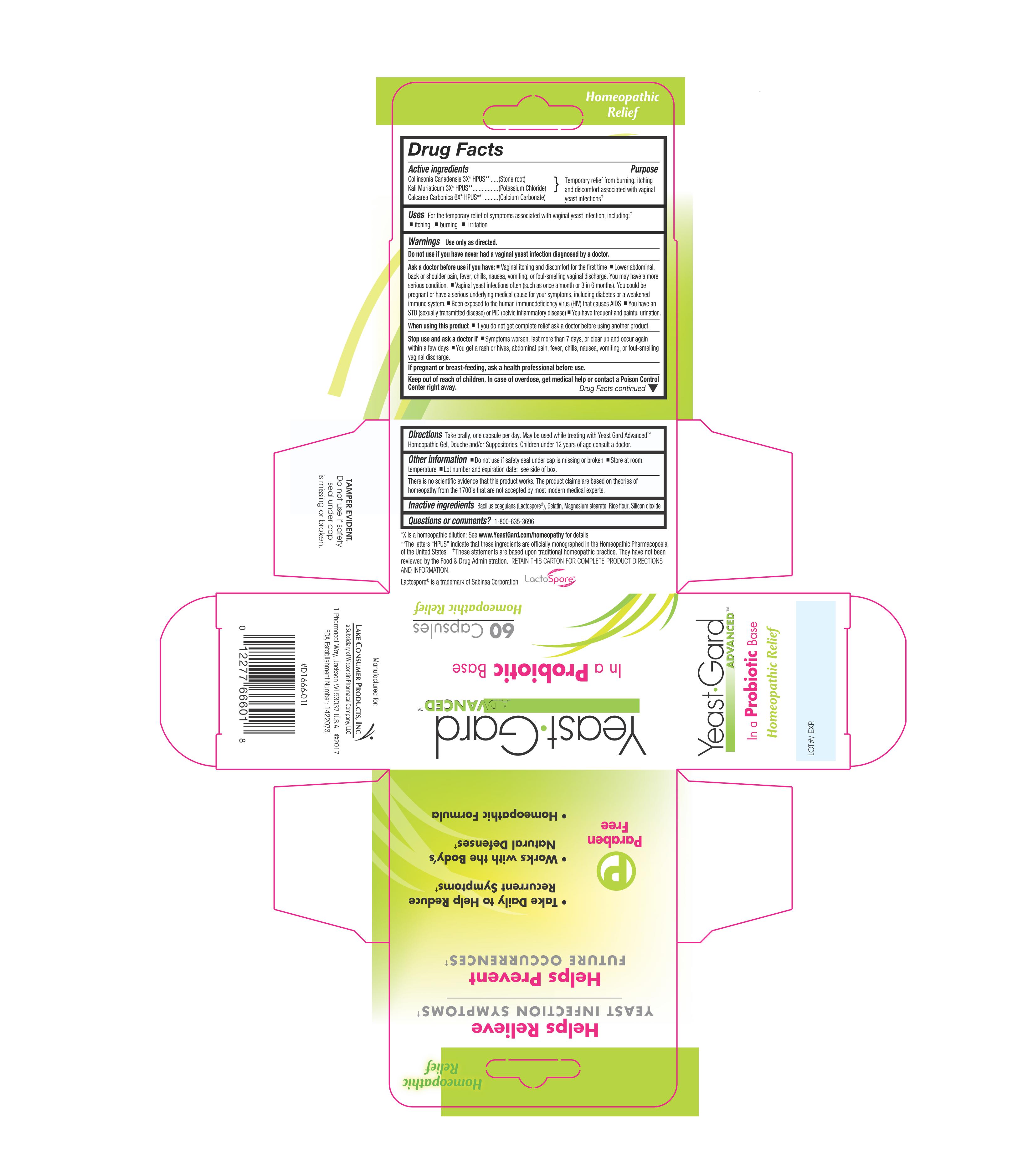 DRUG LABEL: Yeast Gard Advanced
NDC: 68093-6661 | Form: CAPSULE
Manufacturer: Wisconsin Pharmacal Company
Category: homeopathic | Type: HUMAN OTC DRUG LABEL
Date: 20181206

ACTIVE INGREDIENTS: OYSTER SHELL CALCIUM CARBONATE, CRUDE 6 [hp_X]/1 1; COLLINSONIA CANADENSIS ROOT 3 [hp_X]/1 1; POTASSIUM CHLORIDE 3 [hp_X]/1 1
INACTIVE INGREDIENTS: MAGNESIUM STEARATE; BROWN RICE; BACILLUS COAGULANS; GELATIN; SILICON DIOXIDE

Drug Facts

Active Ingredients

Collinsonia Canadensis 3X
Kali Muriaticum 3X
Calcarea Carbonioa 6X

Purpose

Temporary relief from burning, itching and discomfort associated with vaginal yeast infections.

INDICATIONS AND USAGE

Uses For the temporary relief of symptoms associated with vaginal yeast infection, including:

- itching
- buring
- irritation

Warnings Use only as directed

Do not use if you have never had a vaginal yeast infection diagnosed by a doctor.

PREGNANCY OR BREAST FEEDING

If pregnant or breast feeding, ask a health professional before use.

Keep out of reach of children. In case of overdose, get medical help or contact a Poison Control Center right away.

Stop use and ask a doctor if

- Symptoms worsen, last more than 7 days, or clear up and occur again within a few days
- You get a rash or hives, abdominal pain, lever, chills, nausea, vomiting, or foul-smelling vaginal discharge.

Ask a doctor before use if you have:

- Vaginal itching and discomfortlor the first time
- Lower abdominal, back or shoulder pain, fever, chills, nausea, vomiting, ortoul-smelling vaginal discharge. You may have a more

serious condition.

- Vaginal yeast infections often [such as once a month or 3 in 5 months). You could be pregnant or have a serious underlying medical cause lor your symptoms, including diabetes or a weakened immune system.
- Been exposed to the human immunodeficiency virus (Hill) that causes AIDS
- You have an STD (sexually transmitted disease) or PID (pelvic inflammatory disease)
- You have frequent and painful urination.

When using this product

- lf you do not get complete relief ask a doctor before using another product.

DOSAGE AND ADMINISTRATION

Directions Take orally, one capsule per day. May be used while treating with Yeast Gard Advanced
Homeopathic Gel, Douche and/or Suppositories. Children under 12 years of age consult a doctor.

Other information

- Do not use if safety seal under cap is missing or broken
- Store at room temperature
- Lot number and expiration date: see side ol box.

There is no scientific evidence that this product works. The product claims are based on theories of
homeopathy from the 1700's that are not accepted by most modern medical experts.

Inactive Ingredients

Bacillus coagulans, Gelatin, Magnesium stearate, Rice flour, Silicon dioxide

QUESTIONS

Questians or comments? 1-800-635-3696